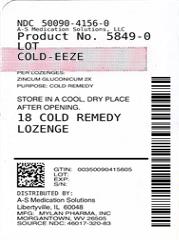 DRUG LABEL: Cold-EEZE
NDC: 50090-4156 | Form: LOZENGE
Manufacturer: A-S Medication Solutions
Category: homeopathic | Type: HUMAN OTC DRUG LABEL
Date: 20190227

ACTIVE INGREDIENTS: ZINC GLUCONATE 2 [hp_X]/1 1
INACTIVE INGREDIENTS: Corn Syrup; Glycine; Sucrose

Drug Facts

Active ingredient (per lozenge)

Zincum Gluconicum 2x

Purpose

Cold Remedy

Uses

- to reduce the duration of the common cold
- reduces the severity of cold symptoms: cough, sore throat, nasal congestion, post nasal drip and/or hoarseness

Warnings

Ask a doctor before use if you

- are taking minocycline, doxycycline, tetracycline or are on Coumadin therapy, zinc treatment may inhibit the absorption of these medicines

Stop use and ask your healthcare practitioner
if symptoms persist beyond 7 days.

Cold-EEZE® lozenges are formulated to reduce the duration of the common cold and its symptoms and is insufficient treatment for Influenza or Allergies.

If pregnant or breastfeeding,

ask a healthcare practitioner before use.

Directions

Adults and children 12 years and over:

- take Cold-EEZE® when you have cold symptoms
- completely dissolve a Cold-EEZE® lozenge in mouth (do not chew)
- repeat every 2 - 4 hours as needed until all symptoms subside
- recommended daily dosage is 6 lozenges for adults and 4 lozenges for ages 12 - 17

Children under 12 years of age should consult a healthcare practitioner prior to use

Other information

- do not take Cold-EEZE® lozenges on an empty stomach to avoid possible minor stomach upset
- do not eat or drink for 15 minutes after use
- store in a cool, dry place after opening; best if used within 6 months after opening
- gluten free

Inactive ingredients

Corn syrup, glycine, natural flavors and sucrose.

No artificial colors or preservatives.

Clinical Studies have shown: The unique Cold-EEZE® formula reduces the duration of the common cold by almost half.

The double blind placebo controlled studies were conducted at the Cleveland Clinic and Dartmouth College and published in peer reviewed journals.

Cold-EEZE® is safe to take with most other medications and is gluten free. (see warnings)

Does Not Cause Drowsiness

Does Not Cause Light Headedness

Does Not Affect Blood Pressure

For cold-fighting tips and more about the Cold-EEZE® science, go to www.ColdEEZE.com

Questions or Comments:

Call 1-800-505-2653
(M-F: 8AM-5PM ET)

Mylan.com

Manufactured for:
Mylan Consumer Healthcare, Inc.
Morgantown, WV 26505 U.S.A.

^+THESE STATEMENTS HAVE NOT BEEN EVALUATED BY THE FOOD AND DRUG ADMINISTRATION. THIS PRODUCT IS NOT INTENDED TO DIAGNOSE, TREAT, CURE OR PREVENT ANY DISEASE.

This product has no expiration date.

HOW SUPPLIED

Product: 50090-4156

NDC: 50090-4156-0 18 LOZENGE in a BAG / 1 in a BOX